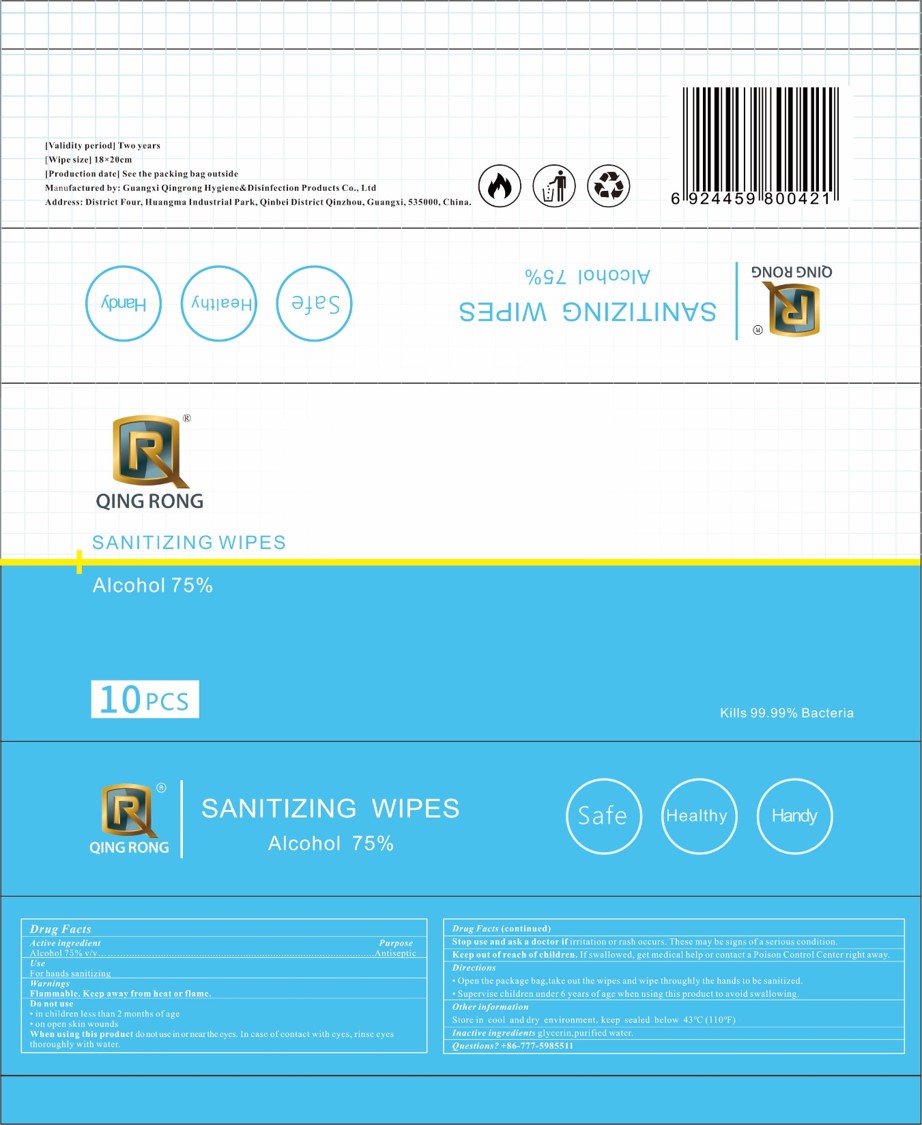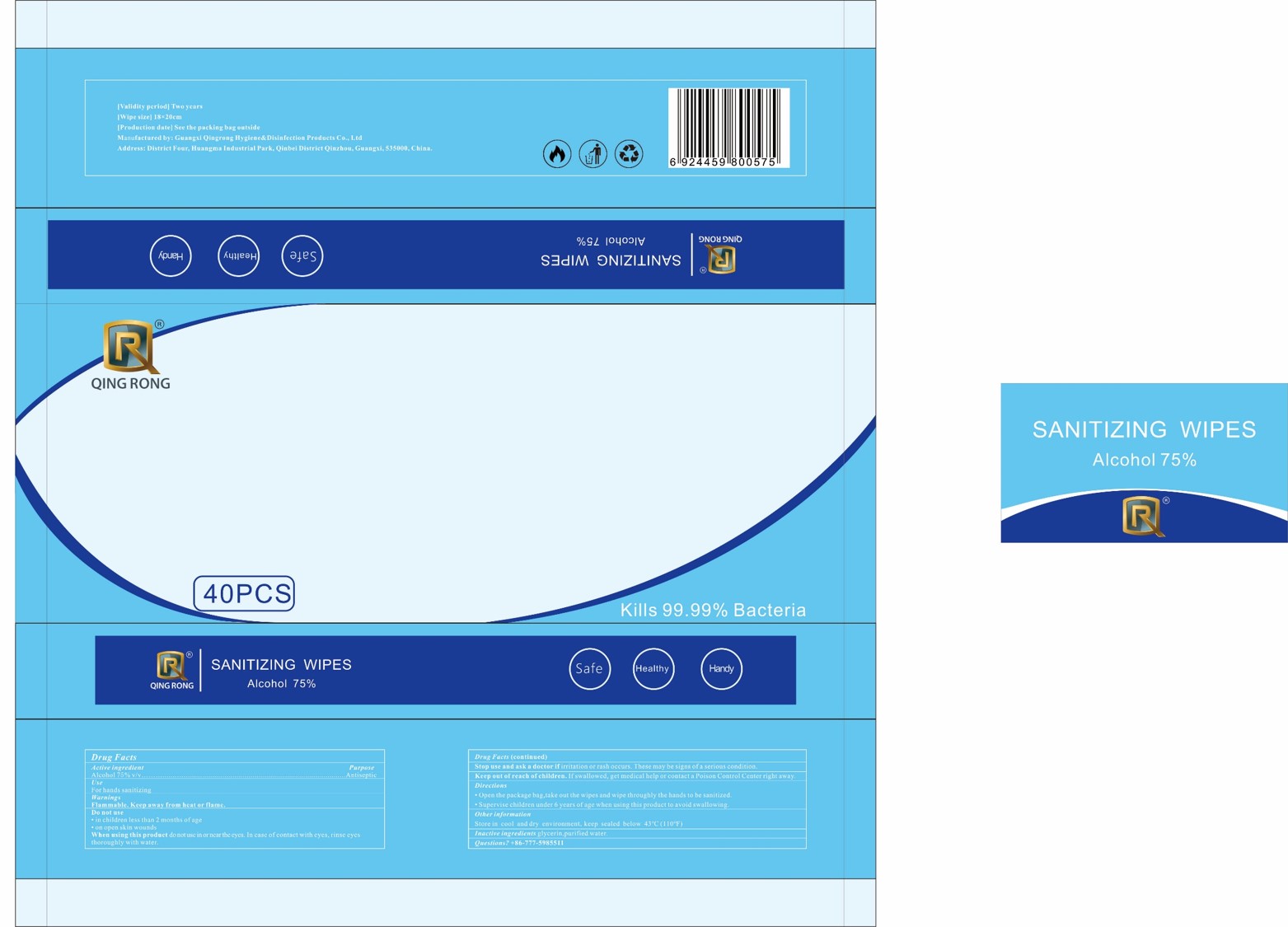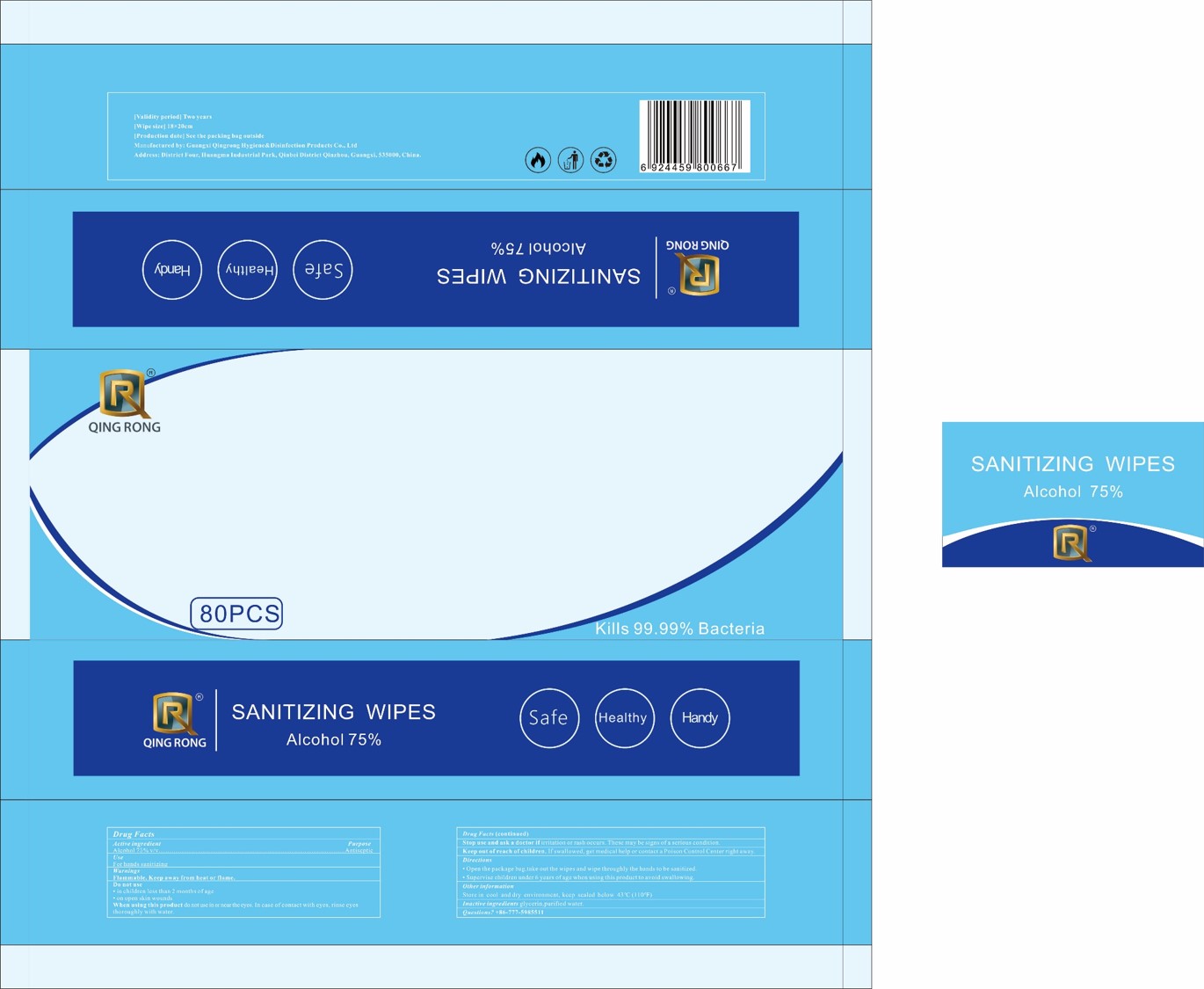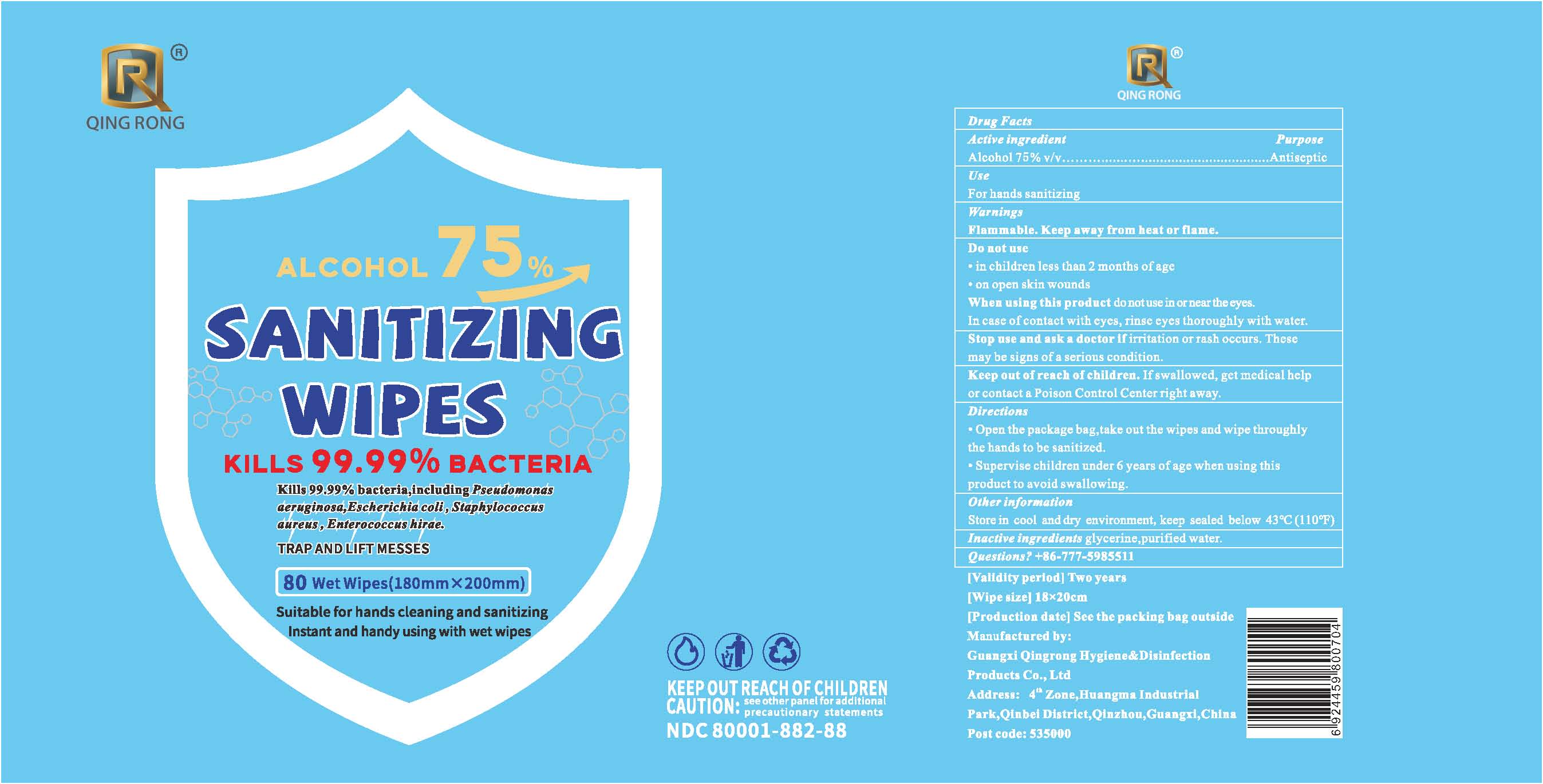 DRUG LABEL: SANITIZING WIPES
NDC: 80001-882 | Form: CLOTH
Manufacturer: Guangxi Qingrong Hygiene&disinfection Products Co.,ltd.
Category: otc | Type: HUMAN OTC DRUG LABEL
Date: 20221208

ACTIVE INGREDIENTS: ALCOHOL 75 g/100 g
INACTIVE INGREDIENTS: GLYCERIN; WATER

Active Ingredient(s)

Alcohol 75% v/v. Purpose: Antiseptic

Purpose

Antiseptic, Hand Sanitizer

Use

For hands sanitizing

Warnings

Flammable. Keep away from heat or flame.

Do not use

- in children less than 2 months of age
- on open skin wounds

When using this product keep out of eyes, ears, and mouth. In case of contact with eyes, rinse eyes thoroughly with water.
Stop use and ask a doctor if irritation or rash occurs. These may be signs of a serious condition.
Keep out of reach of children. If swallowed, get medical help or contact a Poison Control Center right away.

Stop use and ask a doctor if irritation or rash occurs. These may be signs of a serious condition.

Keep out of reach of children. If swallowed, get medical help or contact a Poison Control Center right away.

Directions

- Open the package bag, take out the wipes and wipe throughly the hands to be sanitized.
- Supervise children under 6 years of age when using this product to avoid swallowing.

Other information

- Store in cool and dry environment, keep sealed below 43C(110F）

Inactive ingredients

glycerin, purified water.

Package Label - Principal Display Panel

10 WIPES in 1 BAG NDC: 80001-882-01

Package Label - Principal Display Panel

40 WIPES in 1 BAG NDC: 80001-882-04

Package Label - Principal Display Panel

80 WIPES in 1 BAG NDC: 80001-882-08

Package Label - Principal Display Panel

80 WIPES in 1 PAIL NDC: 80001-882-88